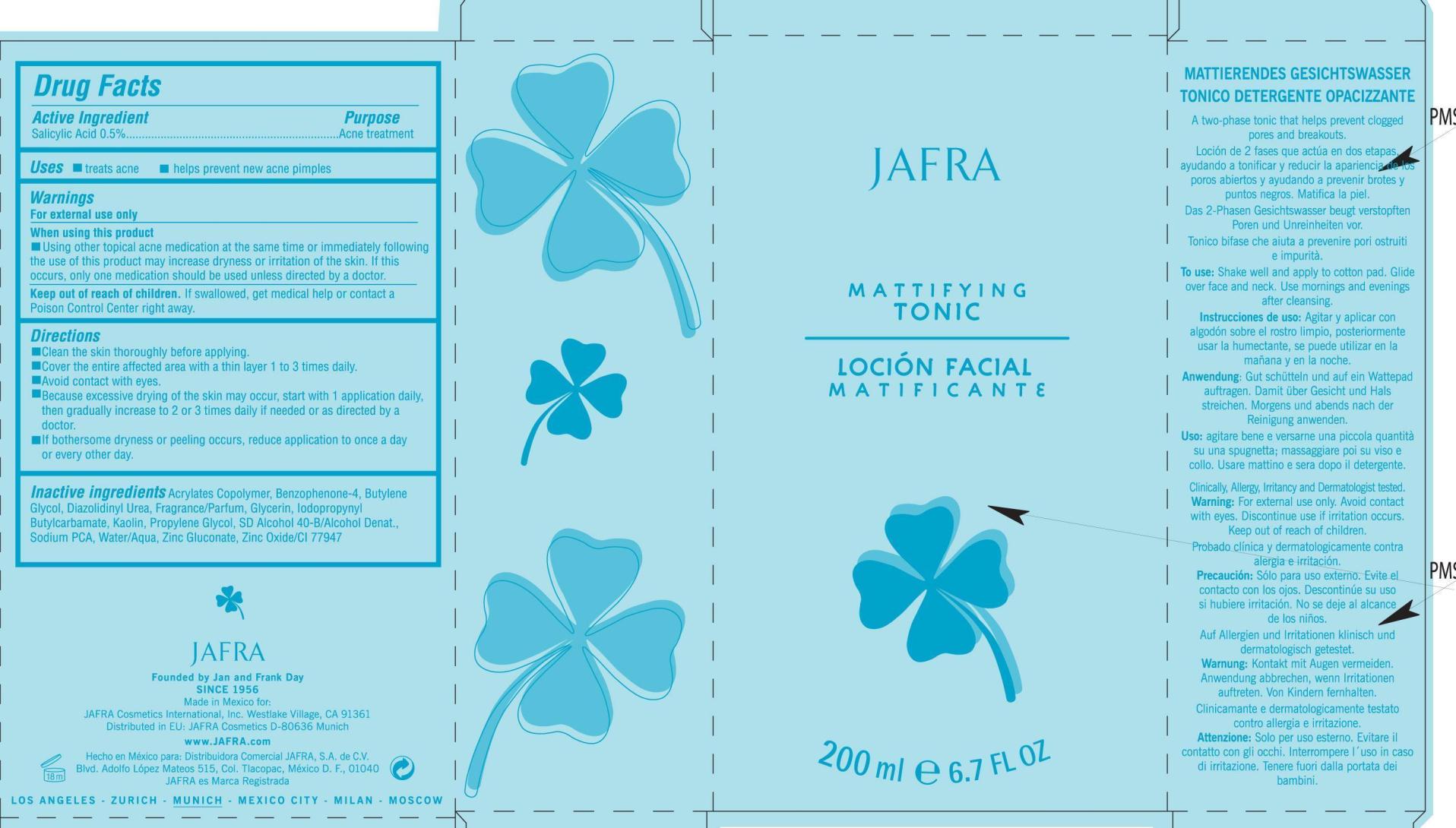 DRUG LABEL: Mattifying Tonic

NDC: 68828-102 | Form: LIQUID
Manufacturer: JAFRA COSMETICS INTERNATIONAL
Category: otc | Type: HUMAN OTC DRUG LABEL
Date: 20200622

ACTIVE INGREDIENTS: SALICYLIC ACID 0.5 g/100 mL
INACTIVE INGREDIENTS: SULISOBENZONE; BUTYLENE GLYCOL; DIAZOLIDINYL UREA; GLYCERIN; IODOPROPYNYL BUTYLCARBAMATE; KAOLIN; PROPYLENE GLYCOL; SODIUM PYRROLIDONE CARBOXYLATE; WATER; ZINC GLUCONATE; ZINC OXIDE

Jafra Mattifying Tonic

Active Ingredients Purpose

Salicylic Acid 0.5% Acne Treatment

PURPOSE

Uses: Treats Acne

Helps prevent new acne pimples

Keep out of reach of children

When using this product

Using other topical acne medication at the same time or immediately following the use of this product may increase dryness or irritation of the skin. If this occurs, only one medication should be used unless directed by a doctor.

Warnings

For external use only.

If swallowed, get medical help or contact a Poison Control Center right away.

Directions
Clean the skin thoroughly before applying.
Cover the entire affected area with a thin layer 1 to 3 times daily.
Avoid contact with eyes
Because excessive drying of the skin may occur, start with 1 application daily, then gradually increase to 2 or 3 times daily if needed or as directed by a doctor.
If bothersome dryness or peeling occurs, reduce application to once a day or every other day.

INACTIVE INGREDIENT

Inactive ingredients: Acrylates Copolymer, Benzophenone-4, Butylene Glycol, Diazolidinyl Urea, Fragrance/parfum, Glycerin, Iodopropynyl Butylcarbamate, Kaolin, Propylene Glycol, SD Alcohol 40-B/Alcohol denat., Sodium PCA, Water/Aqua, Zinc Gluconate, Zinc Oxide/CI77947

PACKAGE LABEL

Jafra Mattifying Tonic
Locion Facial Matificante

200 ml 6.7 Fl Oz